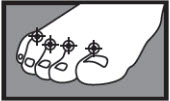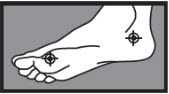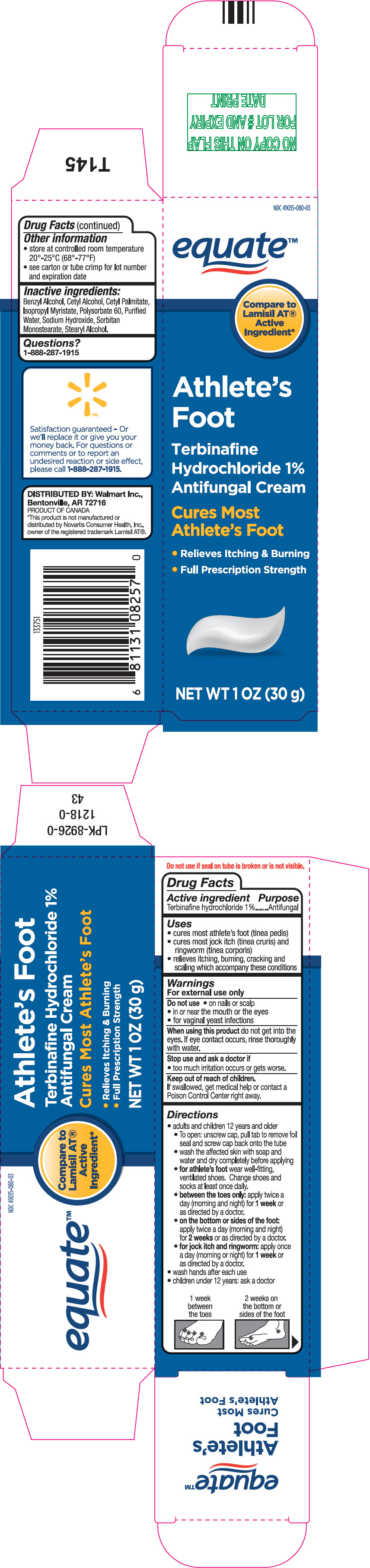 DRUG LABEL: equate 

NDC: 49035-080 | Form: CREAM
Manufacturer: Wal-Mart Stores Inc
Category: otc | Type: HUMAN OTC DRUG LABEL
Date: 20250814

ACTIVE INGREDIENTS: TERBINAFINE HYDROCHLORIDE 1 g/100 g
INACTIVE INGREDIENTS: BENZYL ALCOHOL; CETYL ALCOHOL; CETYL PALMITATE; ISOPROPYL MYRISTATE; POLYSORBATE 60; WATER; SODIUM HYDROXIDE; SORBITAN MONOSTEARATE; STEARYL ALCOHOL

equate™
Athlete's Foot

Drug Facts

Active ingredient

Terbinafine hydrochloride 1%

Purpose

Antifungal

Uses

- cures most athlete's foot (tinea pedis)
- cures most jock itch (tinea cruris) and ringworm (tinea corporis)
- relieves itching, burning, cracking and scaling which accompany these conditions

Warnings

For external use only

Do not use

- on nails or scalp
- in or near the mouth or the eyes
- for vaginal yeast infections

WHEN USING

When using this productdo not get into the eyes. If eye contact occurs, rinse thoroughly with water.

Stop use and ask a doctor if

- too much irritation occurs or gets worse.

Keep out of reach of children.If swallowed, get medical help or contact a Poison Control Center right away.

Directions

- adults and children 12 years and older
  - To open: unscrew cap, pull tab to remove foil seal and screw cap back onto the tube
  - wash the affected skin with soap and water and dry completely before applying
  - for athlete's footwear well-fitting, ventilated shoes. Change shoes and socks at least once daily.
  - between the toes only:apply twice a day (morning and night) for 1 weekor as directed by a doctor.
  - on the bottom or sides of the foot:apply twice a day (morning and night) for 2 weeksor as directed by a doctor.
  - for jock itch and ringworm:apply once a day (morning or night) for 1 weekor as directed by a doctor.
- wash hands after each use
- children under 12 years: ask a doctor

1 week between the toes

2 weeks on the bottom or sides of the foot

Other information

- store at controlled room temperature 20°-25°C (68°-77°F)
- see carton or tube crimp for lot number and expiration date

Inactive ingredients

Benzyl Alcohol, Cetyl Alcohol, Cetyl Palmitate, Isopropyl Myristate, Polysorbate 60, Purified Water, Sodium Hydroxide, Sorbitan Monostearate, Stearyl Alcohol.

Questions?

1-888-287-1915

DISTRIBUTED BY: Walmart Inc.,
Bentonville, AR 72716

PRINCIPAL DISPLAY PANEL - 30 g Tube Carton

NDC 49035-080-03

equate™

Compare to
Lamisil AT®
Active
Ingredient*

Athlete's
Foot

Terbinafine
Hydrochloride 1%
Antifungal Cream

Cures Most
Athlete's Foot

- Relieves Itching & Burning
- Full Prescription Strength

NET WT 1 OZ (30 g)